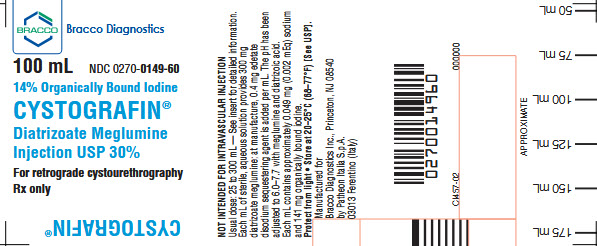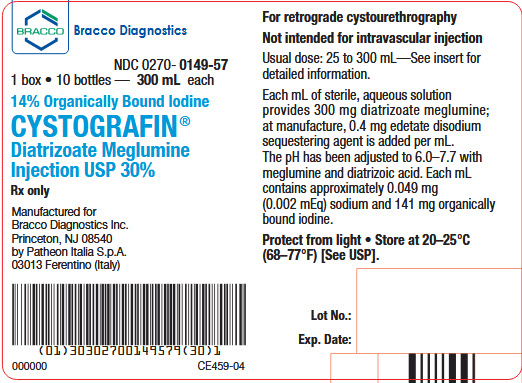 DRUG LABEL: Cystografin
NDC: 0270-0149 | Form: INJECTION, SOLUTION
Manufacturer: BRACCO DIAGNOSTICS INC
Category: prescription | Type: HUMAN PRESCRIPTION DRUG LABEL
Date: 20251123

ACTIVE INGREDIENTS: diatrizoate meglumine 300 mg/1 mL
INACTIVE INGREDIENTS: edetate disodium 0.4 mg/1 mL

CYSTOGRAFIN®
Diatrizoate Meglumine
Injection USP 30%

For retrograde cystourethrography
Not intended for intravascular injection

DESCRIPTION

Cystografin is a radiopaque contrast agent supplied as a sterile, clear, colorless to pale yellow, mobile or slightly viscous solution. Each mL provides 300 mg diatrizoate meglumine with 0.4 mg edetate disodium as a sequestering agent. Each mL of solution also contains approximately 141 mg organically bound iodine. At the time of manufacture, the air in the container is replaced by nitrogen. The preparation should be protected from strong light.

INDICATION

Cystografin is indicated for retrograde cystourethrography.

CONTRAINDICATIONS

This preparation is contraindicated in patients with a hypersensitivity to salts of diatrizoic acid.

WARNINGS

Severe sensitivity reactions are more likely to occur in patients with a personal or family history of bronchial asthma, significant allergies, or previous reactions to contrast agents.

A history of sensitivity to iodine per se or to other contrast agents is not an absolute contraindication to the use of diatrizoate meglumine, but calls for extreme caution in administration.

PRECAUTIONS

Safe and effective use of this preparation depends upon proper dosage, correct technique, adequate precautions, and readiness for emergencies.

Retrograde cystourethrography should be performed with caution in patients with a known active infectious process of the urinary tract.

Sterile technique should be employed in administration. During administration, care should be taken to avoid excessive pressure, rapid or acute distention of the bladder, and trauma.

Contrast agents may interfere with some chemical determinations made on urine specimens; therefore, urine should be collected before administration of the contrast medium or two or more days afterwards.

Pregnancy—Teratogenic Effects:

Animal reproduction studies have not been conducted with diatrizoate meglumine injection. It is also not known whether diatrizoate meglumine injection can cause fetal harm when administered to a pregnant woman or can affect reproduction capacity. Cystografin should be administered to a pregnant woman only if clearly needed.

ADVERSE REACTIONS

Retrograde genitourinary procedures may cause such complications as hematuria, perforation of the urethra or bladder, introduction of infection into the genitourinary tract, and oliguria or anuria.

If intravasation of this drug occurs, the reactions which may be associated with intravenous administration may possibly be encountered. Hypersensitivity or anaphylactoid reactions may occur. Severe reactions may be manifested by edema of the face and glottis, respiratory distress, convulsions or shock; such reactions may prove fatal unless promptly controlled by such emergency measures as maintenance of a clear airway and immediate use of oxygen and resuscitative drugs.

Endocrine: Thyroid function tests indicative of hypothyroidism or transient thyroid suppression have been uncommonly reported following iodinated contrast media administration to adult and pediatric patients, including infants. Some patients were treated for hypothyroidism.

DOSAGE AND ADMINISTRATION

Preparation of the patient: Appropriate preparation is desirable for optimal results. A laxative the night before the examination and a low residue diet the day before the procedure are recommended.

Dosage: The dose for retrograde use in cystography and voiding cystourethrography ranges from 25 to 300 mL depending on the age of the patient and the degree of bladder irritability; amounts greater than 300 mL may be used if the bladder capacity allows. Best results are obtained when the bladder is filled with the contrast agent. If desired, the preparation may be diluted with sterile water or sterile saline as indicated in the table below.

Administration: After sterile catheterization, the bladder should be filled to capacity with Cystografin using a suitable sterile administration set. Care should be taken to avoid using excessive pressure. The presence of bladder discomfort or reflux and/or spontaneous voiding usually indicates that the bladder is full.

Radiography: The commonly employed radiographic techniques should be used. A scout film is recommended before the contrast agent is administered.

Dilution Table
USE DILUTED SOLUTIONS IMMEDIATELY
100 mL Bottle
Sterile Water or Sterile Saline Added | % Diatrizoate Meglumine w/v | % Organically Bound Iodine w/v | Total Volume
0 mL | 30.0 | 14.1 | 100 mL
25 mL | 24.0 | 11.3 | 125 mL
50 mL | 20.0 | 9.4 | 150 mL
67 mL | 18.0 | 8.5 | 167 mL
300 mL Bottle
Sterile Water or Sterile Saline Added
0 mL | 30.0 | 14.1 | 300 mL
50 mL | 25.7 | 12.1 | 350 mL

HOW SUPPLIED

Cystografin (Diatrizoate Meglumine Injection USP 30%) is available in 200 mL and 400 mL bottles containing 100 mL and 300 mL of Cystografin respectively with sufficient capacity for dilution up to 167 mL and 350 mL respectively.

Storage

Store at 20-25°C (68-77°F) [See USP]. Protect from light.

Also Available

Cystografin Dilute (Diatrizoate Meglumine Injection USP 18%) is also available, as a 300 mL fill in a 400 mL bottle.

Rx only

Manufactured for
Bracco Diagnostics Inc.
Princeton, NJ 08540

by Patheon Italia S.p.A.
03013 Ferentino (Italy)

Revised June 2024

Cystografin 100 mL Label
NDC 0270-0149-60

Cystografin 1 Box 10 Bottles — 300 mL each
NDC 0270-0149-57